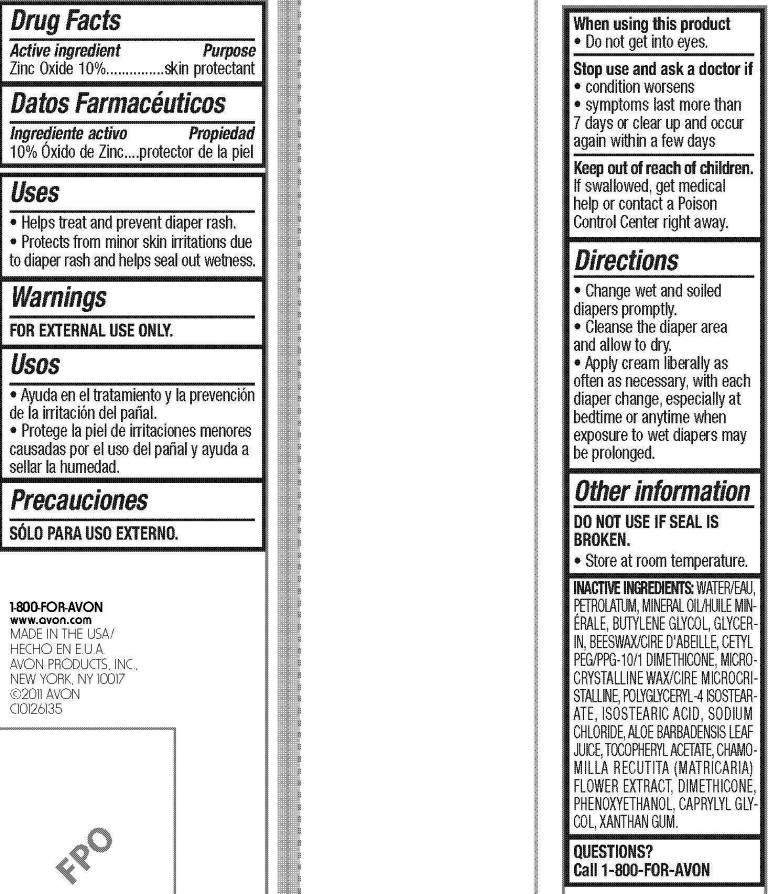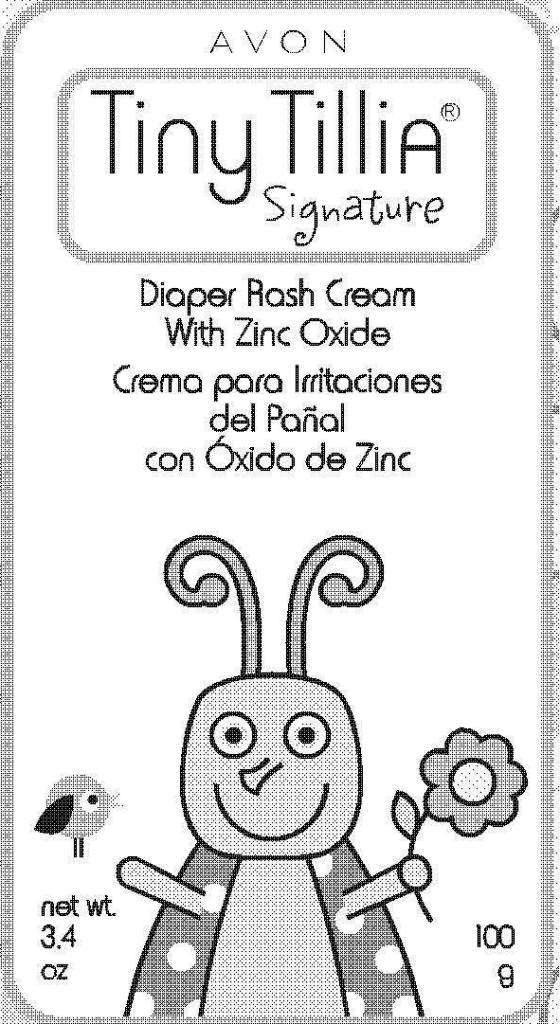 DRUG LABEL: Tiny Tillia
NDC: 10096-0242 | Form: CREAM
Manufacturer: Avon Products, Inc.
Category: otc | Type: HUMAN OTC DRUG LABEL
Date: 20110126

ACTIVE INGREDIENTS: ZINC OXIDE	 10 g/100 g
INACTIVE INGREDIENTS: WATER	; PETROLATUM	; MINERAL OIL	; BUTYLENE GLYCOL	; GLYCERIN	; MICROCRYSTALLINE WAX	; POLYGLYCERYL-4 ISOSTEARATE	; ISOSTEARIC ACID	; SODIUM CHLORIDE	; DIMETHICONE	; PHENOXYETHANOL	; CAPRYLYL GLYCOL	; XANTHAN GUM	

Drug Facts

Active Ingredient
Zinc Oxide 10%...........................

Purpose

.......................skin protectant

Uses

- Helps treat and prevent diaper rash.
- Protects from minor skin irritations due to diaper rash and helps seal out wetness.

Directions

- Change wet and soiled diapers promptly.
- Cleanse the diaper area and allow to dry.
- Apply cream liberally as often as necessary, with each diaper change, especially at bedtime or anytime when exposure to wet diapers may be prolonged.

Inactive ingredients

WATER/EAU
PETROLATUM
MINERAL OIL/HUILE MINERALE
BUTYLENE GLYCOL
GLYCERIN
BEESWAX/CIRE D'ABEILLE
CETYL PEG/PPG-10/1 DIMETHICONE
MICROCRYSTALLINE WAX/CIRE MICROCRISTALLINE
POLYGLYCERYL-4 ISOSTEARATE
ISOSTEARIC ACID
SODIUM CHLORIDE
ALOE BARBADENSIS LEAF JUICE
TOCOPHERYL ACETATE
CHAMOMILLA RECUTITA (MATRICARIA) FLOWER EXTRACT
DIMETHICONE
PHENOXYETHANOL
CAPRYLYL GLYCOL
XANTHAN GUM

QUESTIONS? Call 1-800-FOR-AVON

Warnings
FOR EXTERNAL USE ONLY.

When using this product
• Do not get into eyes.

Stop use and ask a doctor if
• condition worsens
• symptoms last more than
7 days or clear up and occur
again within a few days

Keep out of reach of children.
If swallowed, get medical
help or contact a Poison
Control Center right away.

Other information
DO NOT USE IF SEAL IS
BROKEN.
• Store at room temperature.